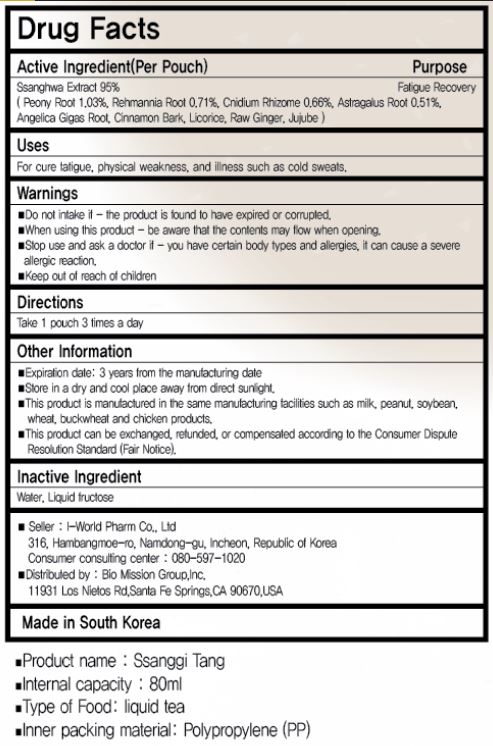 DRUG LABEL: SSANGGI TANG
NDC: 73442-0009 | Form: LIQUID
Manufacturer: I World Pharmaceutical Co., Ltd.
Category: otc | Type: HUMAN OTC DRUG LABEL
Date: 20250212

ACTIVE INGREDIENTS: PAEONIA LACTIFLORA ROOT 0.9785 g/100 mL; REHMANNIA GLUTINOSA ROOT 0.6745 g/100 mL; LIGUSTICUM SINENSE SUBSP. CHUANXIONG ROOT 0.627 g/100 mL; ASTRAGALUS GUMMIFER ROOT 0.4845 g/100 mL
INACTIVE INGREDIENTS: FRUCTOSE; WATER

ACTIVE INGREDIENT

ssanghwa extract (peony root, rehmannia root, cnidium rhizome, astragalus root, angelica gias root, cinnamon bark, licorice, raw ginger, jujube)

PURPOSE

for cure fatigue, physical weakness, and illness such as cold sweats

Keep out of reach of children

INDICATIONS AND USAGE

take 1 pouch 3 times a day

WARNINGS

do not intake if the product is found to have expired or corrupted

when using this product be aware that the contents may flow when opening

stop use and ask a doctor if you have certain body types and allergies, it can cause a severe allergic reaction

INACTIVE INGREDIENT

water, liquid fructose

DOSAGE AND ADMINISTRATION

For oral use only